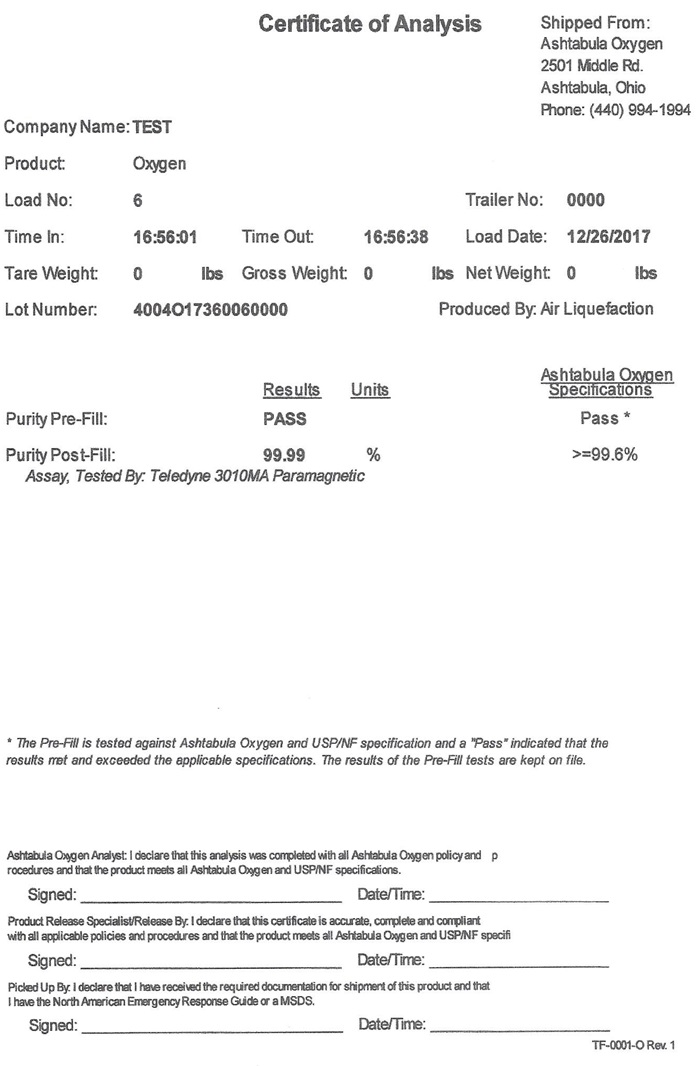 DRUG LABEL: Oxygen
NDC: 71408-001 | Form: GAS
Manufacturer: Ineos Pigments ASU LLC
Category: prescription | Type: HUMAN PRESCRIPTION DRUG LABEL
Date: 20241027

ACTIVE INGREDIENTS: OXYGEN 99 L/100 L

Oxygen

Oxygen COA

Certificate of Analysis Shipped From:

Ashtabula Oxygen

2501 Middle Rd.

Ashtabula, Ohio

Phone: (440) 994-1994

Company Name: TEST

Product: Oxygen

Load No: 6 Trailer No: 0000

Time In: 16:56:01 Time Out: 16:56:38 Load Date: 12/26/2017

Tare Weight: 0 Gross Weight: 0 lbs Net Weight: 0 lbs

Lot Number: 4004O17360060000 Produced by: Air Liquefaction

Ashtabula Oxygen

Results Units Specifications

Purity Pre-Fill: PASS Pass*

Purity Post-Fill: 99.99 % >=99.6%

Assay, Tested By: Teledyne 3010MA Paramagnetic

- The Pre-Fill is tested against Ashtabula Oxygen and USP/NF specification and a “Pass” indicated that the results met and exceeded the applicable specifications. The results of the Pre-Fill tests are kept on file.

Ashtabula Oxygen Analyst: I declare that this analysis was completed with all Ashtabula Oxygen policy and procedures and that the product meets all Ashtabula Oxygen and USP/NF specifications.

Signed: Date/Time:

Product Release Specialist/Release By: I declare that this certification is accurate, complete and compliant with all applicable policies and procedures and that the product meets all Ashtabula Oxygen and USP/NF specifications.

Signed: Date/Time:

Picked Up By: I declare that I have received the required documentation for shipment of this product and that I have the North American Emergency Response Guide or a MSDS.

Signed: Date/Time:

TF-0001-O Rev.1